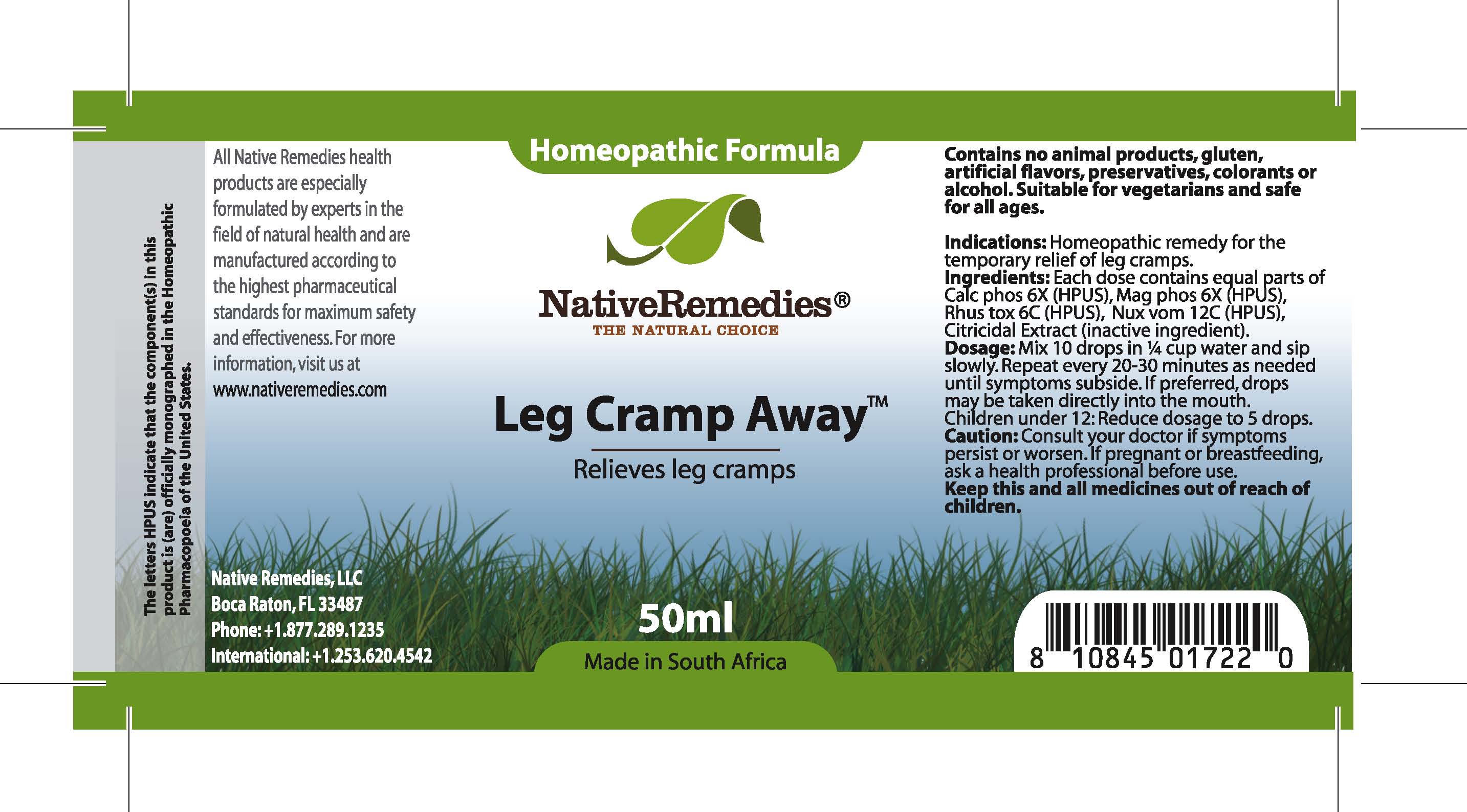 DRUG LABEL: Leg Cramp Away
NDC: 68647-170 | Form: TINCTURE
Manufacturer: Feelgood Health
Category: homeopathic | Type: HUMAN OTC DRUG LABEL
Date: 20100727

ACTIVE INGREDIENTS: TRIBASIC CALCIUM PHOSPHATE 6 [hp_X]/ 50 mL; MAGNESIUM PHOSPHATE, DIBASIC TRIHYDRATE 6 [hp_X]/50 mL; TOXICODENDRON PUBESCENS LEAF 6 [hp_C]/50 mL; STRYCHNOS NUX-VOMICA SEED 12 [hp_C]/50 mL
INACTIVE INGREDIENTS: CITRUS PARADISI SEED 0.125 mL/50 mL; WATER 49.486 mL/50 mL

LEG CRAMP AWAY

PURPOSE

Relieves leg cramps

INDICATIONS AND USAGE

Indications: Homeopathic remedy for the relief of leg cramps.

DOSAGE AND ADMINISTRATION

Dosage: Mix 10 drops in ¼ cup water and sip slowly. Repeat every 20-30 minutes as needed until symptoms subside. If preferred, drops may be taken directly into the mouth. Children under 12: Reduce dosage to 5 drops.

GENERAL PRECAUTIONS

Caution: Consult your doctor if symptoms persist or worsen.

ACTIVE INGREDIENT

Ingredients: Each dose contains equal parts of Calc phos (6X) (HPUS), Mag phos (6X) (HPUS), Rhus tox (6C) (HPUS), Nux vom (12C) (HPUS)

Citricidal extract (inactive ingredient)

PREGNANCY

If pregnant or breastfeeding, ask a health professional before use.

WARNINGS

Contains no animal products, gluten, artificial flavors, preservatives, colorants or alcohol. Suitable for vegetarians and safe for all ages.

PATIENT COUNSELING INFORMATION

All Native Remedies health products are especially formulated by experts in the field of natural health and are manufactured according to the highest pharmaceutical standards for maximum safety and effectiveness. For more information, visit us at www.nativeremedies.com

Distributed by

Native Remedies, LLC

6531 Park of Commerce Blvd.

Suite 160

Boca Raton, FL 33487

Phone: 1.877.289.1235

International: + 1.561.999.8857

The letters HPUS indicate that the component(s) in this product is (are) officially monographed in the Homeopathic Pharmacopoeia of the United States.

KEEP OUT OF REACH OF CHILDREN

Keep this and all medications out of reach of children.